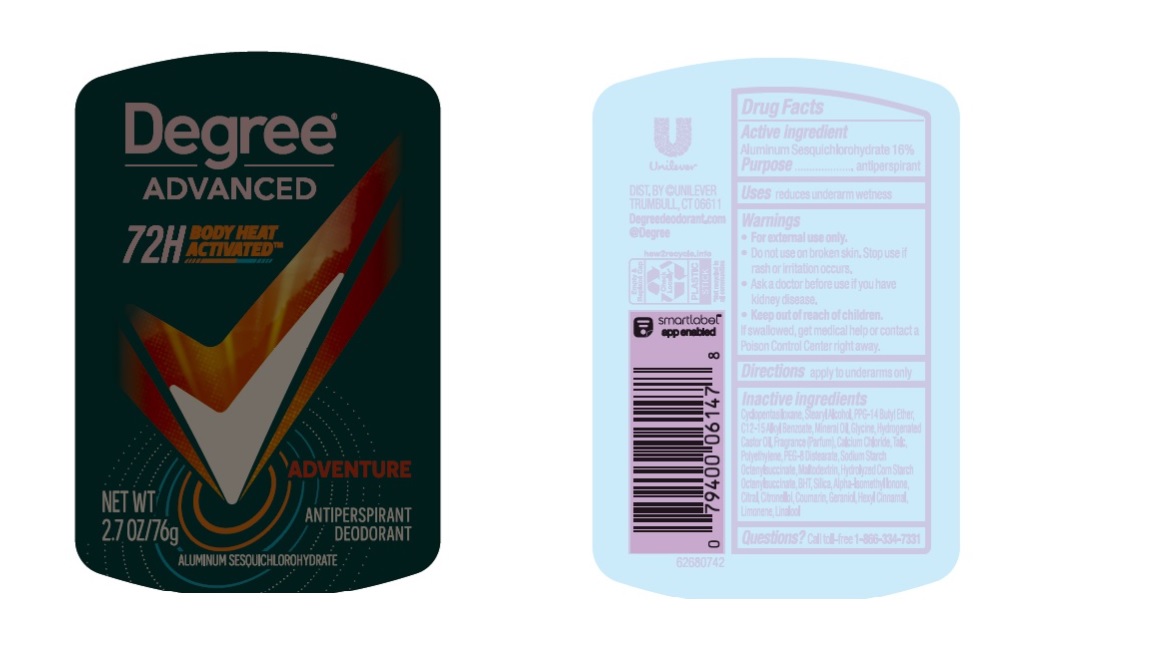 DRUG LABEL: Degree
NDC: 64942-2215 | Form: STICK
Manufacturer: Conopco Inc. d/b/a/ Unilever
Category: otc | Type: HUMAN OTC DRUG LABEL
Date: 20230919

ACTIVE INGREDIENTS: ALUMINUM ZIRCONIUM TETRACHLOROHYDREX GLY 18.2 g/100 g
INACTIVE INGREDIENTS: COUMARIN; LINALOOL, (+/-)-; MINERAL OIL; HYDROGENATED CASTOR OIL; CYCLOMETHICONE 5; BUTYLATED HYDROXYTOLUENE; PEG-8 DISTEARATE; TALC; PPG-14 BUTYL ETHER; STEARYL ALCOHOL; .BETA.-CITRONELLOL, (R)-; GLYCINE; CITRAL; ALKYL (C12-15) BENZOATE; LIMONENE, (+)-; ISOMETHYL-.ALPHA.-IONONE; GERANIOL; .ALPHA.-HEXYLCINNAMALDEHYDE; CALCIUM CHLORIDE; SILICON DIOXIDE; MALTODEXTRIN; HIGH DENSITY POLYETHYLENE

Degree Advanced Adventure 72H Antiperspirant Deodorant

Drug Facts

Active ingredient

Aluminum Zirconium Tetrachlorohydrex GLY (18.2 %)

Purpose

antiperspirant

Uses

reduces underarm wetness

Warnings

• For external use only

• Do not use on broken skin
• Stop use if rash or irritation occurs
• Ask a doctor before use if you have kidney disease

.

• Keep out of reach of children.

If swallowed, get medical help or contact a Poison Control Center right away.

Directions

apply to underarms only

Inactive ingredients

Cyclopentasiloxane, Stearyl Alcohol, PPG-14 Butyl Ether, C12-15 Alkyl Benzoate, Mineral Oil, Glycine, Hydrogenated Castor Oil, Fragrance (Parfum), Calcium Chloride, Talc, Polyethylene, PEG-8 Distearate, Sodium Starch Octenylsuccinate, Maltodextrin, Hydrolyzed Corn Starch Octenylsuccinate, BHT, Silica, Alpha-Isomethyl Ionone, Citral, Citronellol, Coumarin, Geraniol, Hexyl Cinnamal, Limonene. Linalool

Questions?

Call toll-free 1-866-334-7331